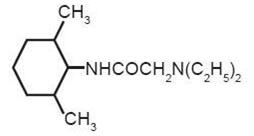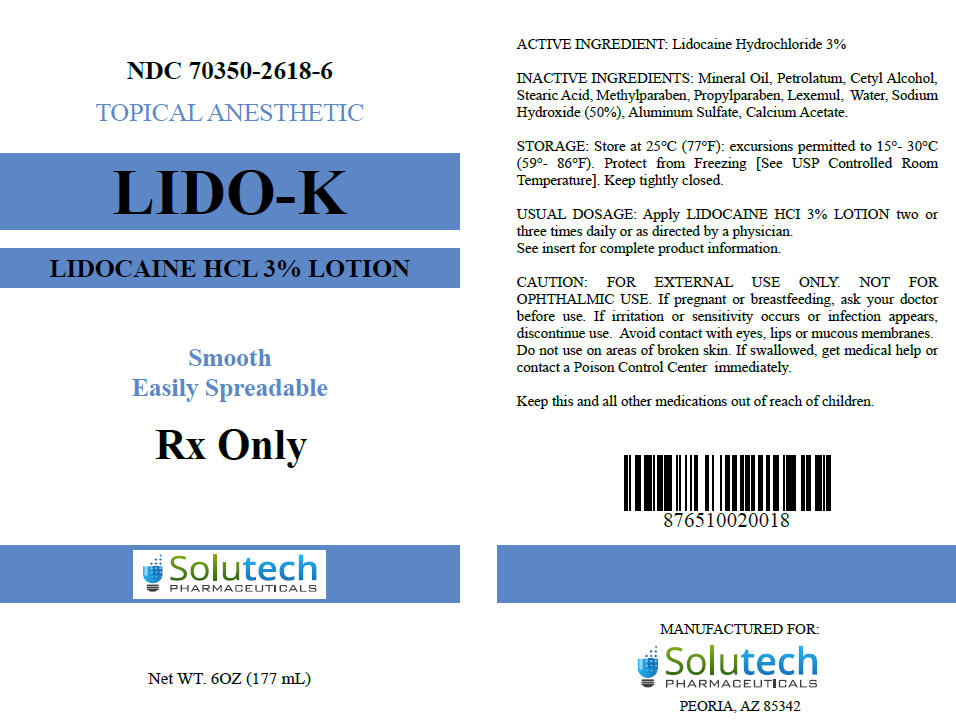 DRUG LABEL: LIDO-K
NDC: 70350-2618 | Form: LOTION
Manufacturer: SOLUTECH PHARMACEUTICALS LLC
Category: prescription | Type: HUMAN PRESCRIPTION DRUG LABEL
Date: 20180207

ACTIVE INGREDIENTS: LIDOCAINE HYDROCHLORIDE 30 mg/1 mL
INACTIVE INGREDIENTS: SODIUM HYDROXIDE; MINERAL OIL; PETROLATUM; CETYL ALCOHOL; STEARIC ACID; METHYLPARABEN; PROPYLPARABEN; GLYCERYL DILAURATE; WATER; ALUMINUM SULFATE; CALCIUM ACETATE

Lido-K
(Lidocaine Hydrochloride 3% Lotion)

Topical Anesthetic

For external use only.
Not for ophthalmic use.

Rx only

DESCRIPTION

Contains Lidocaine Hydrochloride. Lidocaine is chemically designated as acetamide, 2-(diethylamino)-N-(2,6-dimethylphenyl), and has the following structure:

C14H22N2O

Each mL of Lido-K Lotion contains ACTIVE: Lidocaine HCl 30 mg in a lotion base of INACTIVES: Mineral Oil, Petrolatum, Cetyl Alcohol, Stearic Acid, Methylparaben, Propylparaben, Lexemul, Water, Sodium Hydroxide (50%), Aluminum Sulfate, and Calcium Acetate

CLINICAL PHARMACOLOGY

MECHANISM OF ACTION

Lidocaine stabilizes the neuronal membrane by inhibiting the ionic fluxes required for initiation and conduction of impulses, thereby effecting local anesthetic action.

PHARMACOKINETICS

Lidocaine may be absorbed following topical administration to mucous membranes, its rate and extent of absorption depending upon the specific site of application, duration of exposure, concentration and total dosage. In general, the rate of absorption of local anesthetic agents following topical application occurs most rapidly after intratracheal administration. Lidocaine is also well-absorbed from the gastrointestinal tract, but little intact drug appears in the circulation because of biotransformation in the liver.

Lidocaine is metabolized rapidly by the liver, and metabolites and unchanged drug are excreted by the kidneys. Biotransformation includes oxidative N-dealkylation, ring hydroxylation, cleavage of the amide linkage, and conjugation. N-dealkylation, a major pathway of biotransformation, yields the metabolites monoethylglycinexylidide and glycinexylidide. The pharmacological / toxicological actions of these metabolites are similar to, but less potent than, those of Lidocaine. Approximately 90% of Lidocaine administered is excreted in the form of various metabolites, and less than 10% is excreted unchanged. The primary metabolite in urine is a conjugate of 4-hydroxy-2,6-dimethylaniline.

The plasma binding of Lidocaine is dependent on drug concentration, and the fraction bound decreases with increasing concentration. At concentrations of 1-4 g of free base per mL, 60 to 80 percent of Lidocaine is protein bound. Binding is also dependent on the plasma concentration of the alpha-1-acid glycoprotein.

Lidocaine crosses the blood-brain and placental barriers, presumably by passive diffusion.

Studies of Lidocaine metabolism following intravenous bolus injections have shown that the elimination half-life of this agent is typically 1.5 to 2 hours. Because of the rapid rate at which Lidocaine is metabolized, any condition that affects liver function may alter Lidocaine kinetics. The half-life may be prolonged two-fold or more in patients with liver dysfunction. Renal dysfunction does not affect Lidocaine kinetics but may increase the accumulation of metabolites.

Factors such as acidosis and the use of CNS stimulants and depressants affect the CNS levels of Lidocaine required to produce overt systemic effects. Objective adverse manifestations become increasingly apparent with increasing venous plasma levels above 6 g free base per mL. In the rhesus monkey, arterial blood levels of 18-21 g/ml have been shown to be threshold for convulsive activity.

INDICATIONS

Topical anesthetic for use on intact skin for pain and local analgesic.

CONTRAINDICATIONS

Traumatized mucosa, secondary bacterial infection of the area of proposed application and known hypersensitivity to any of the components. Lido-K is contraindicated in patients with a known history of hypersensitivity to local anesthetics of the amide type or to any other component of the product.

WARNINGS

For external use only. Not for ophthalmic use. Avoid contact with eyes, lips or mucous membranes. Do not use on areas of broken skin. If irritation or sensitivity occurs or infection appears, discontinue use. If swallowed, get medical help or contact a Poison Control Center right away.

Application of lidocaine to larger areas or for longer times than those recommended could result in sufficient absorption of lidocaine resulting in serious adverse effects.

Patients treated with class III anti-arrhythmic drugs (e.g., amiodarone, bretylium, sotalol, dofetilide) should be under close surveillance and ECG monitoring considered, because cardiac effects may be additive.

Lidocaine should be used with extreme caution in the presence of sepsis or severely traumatized mucosa in the area of application, since under such conditions there is the potential for rapid systemic absorption.

PRECAUTIONS

If irritation or sensitivity occurs or infection appears, discontinue treatment and institute appropriate therapy. Lido-K should be used with caution in ill, elderly, debilitated patients and children who may be more sensitive to the systemic effects of lidocaine.

CARCINOGENESIS, MUTAGENESIS AND IMPAIRMENT OF FERTILITY

Studies of Lidocaine in animals to evaluate the carcinogenic and mutagenic potential of the effect on fertility have not been conducted.

USE IN PREGNANCY

Teratogenic Effects

Pregnancy Category B

Reproduction studies have been performed in rats at doses up to 6.6 times the human dose and have revealed no evidence of harm to the fetus caused by Lidocaine. There are, however, no adequate and well controlled studies in pregnant women. Animal reproduction studies are not always predictive of human response. General consideration should be given to this fact before administering Lidocaine to women of childbearing potential, especially during early pregnancy when maximum organogenesis takes place.

Lidocaine does pass very quickly through the placenta so doctors and experts suggest only using the anesthetic for established medical needs only as directed by your physician.

NURSING MOTHERS

It is not known whether this drug is excreted in human milk. Because many drugs are excreted in human milk, caution should be exercised when this drug is administered to a nursing mother. Your doctor and you will decide if the benefits outweigh the risk of using lidocaine.

PEDIATRIC USE

Dosage in pediatric patients would be reduced commensurate with age, body weight and physical condition.

If your child becomes very dizzy, excessively sleepy, or develops duskiness of the face or lips after applying lidocaine lotion, remove the lotion and contact your physician at once.

ADVERSE REACTIONS

During or immediately after treatment, the skin at the site of treatment may develop erythema or edema or maybe the locus of abnormal sensation.

Adverse experiences following the administration of lidocaine are similar in nature to those observed with other amide local anesthetic agents. These adverse experiences are, in general, dose-related and may result from high plasma levels caused by excessive dosage or rapid absorption, or may result from a hypersensitivity, idiosyncrasy or diminished tolerance on the part of the patient. Serious adverse experiences are generally systemic in nature. The following types are those most commonly reported:

Central nervous system

CNS manifestations are excitatory and/or depressant and may be characterized by lightheadedness, nervousness, apprehension, euphoria, confusion, dizziness, drowsiness, tinnitus, blurred or double vision, vomiting, sensations of heat, cold or numbness, twitching, tremors, convulsions, unconsciousness, respiratory depression and arrest. The excitatory manifestations may be very brief or may not occur at all, in which case the first manifestation of toxicity may be drowsiness merging into unconsciousness and respiratory arrest. Drowsiness following the administration of lidocaine is usually an early sign of a high blood level of the drug and may occur as a consequence of rapid absorption.

Cardiovascular system

Cardiovascular manifestations are usually depressant and are characterized by bradycardia, hypotension, and cardiovascular collapse, which may lead to cardiac arrest.

Allergic

Allergic reactions are characterized by cutaneous lesions, urticaria, edema or anaphylactoid reactions. Allergic reactions may occur as a result of sensitivity either to the local anesthetic agent or to other components in the formulation. Allergic reactions as a result of sensitivity to lidocaine are extremely rare and, if they occur, should be managed by conventional means. The detection of sensitivity by skin testing is of doubtful value.

DOSAGE AND ADMINISTRATION

Apply a thin film to the affected area two or three times daily or as directed by a physician.

Caution should be exercised, particularly when employing large amounts, since the incidence of adverse effects is directly proportional to the total dose of local anesthetic agent administered.

HOW SUPPLIED

Lido-K Lotion is supplied in the following size:

Size | NDC#
6oz (177 mL) Bottle | 70350-2618-6

KEEP THIS AND ALL MEDICATION OUT OF THE REACH OF CHILDREN.

STORAGE

Store at 25°C (77°F); excursions permitted to 15° - 30°C (59° - 86°F). Protect from freezing [See USP Controlled Room Temperature].

Manufactured for:
Solutech Pharmaceuticals LLC
Peoria, AZ 85345

Rx only

PRINCIPAL DISPLAY PANEL - 177 mL Bottle Label

NDC 70350-2618-6

TOPICAL ANESTHETIC

LIDO-K

LIDOCAINE HCL 3% LOTION

Smooth
Easily Spreadable

Rx Only

Solutech
PHARMACEUTICALS

Net WT. 6OZ (177 mL)